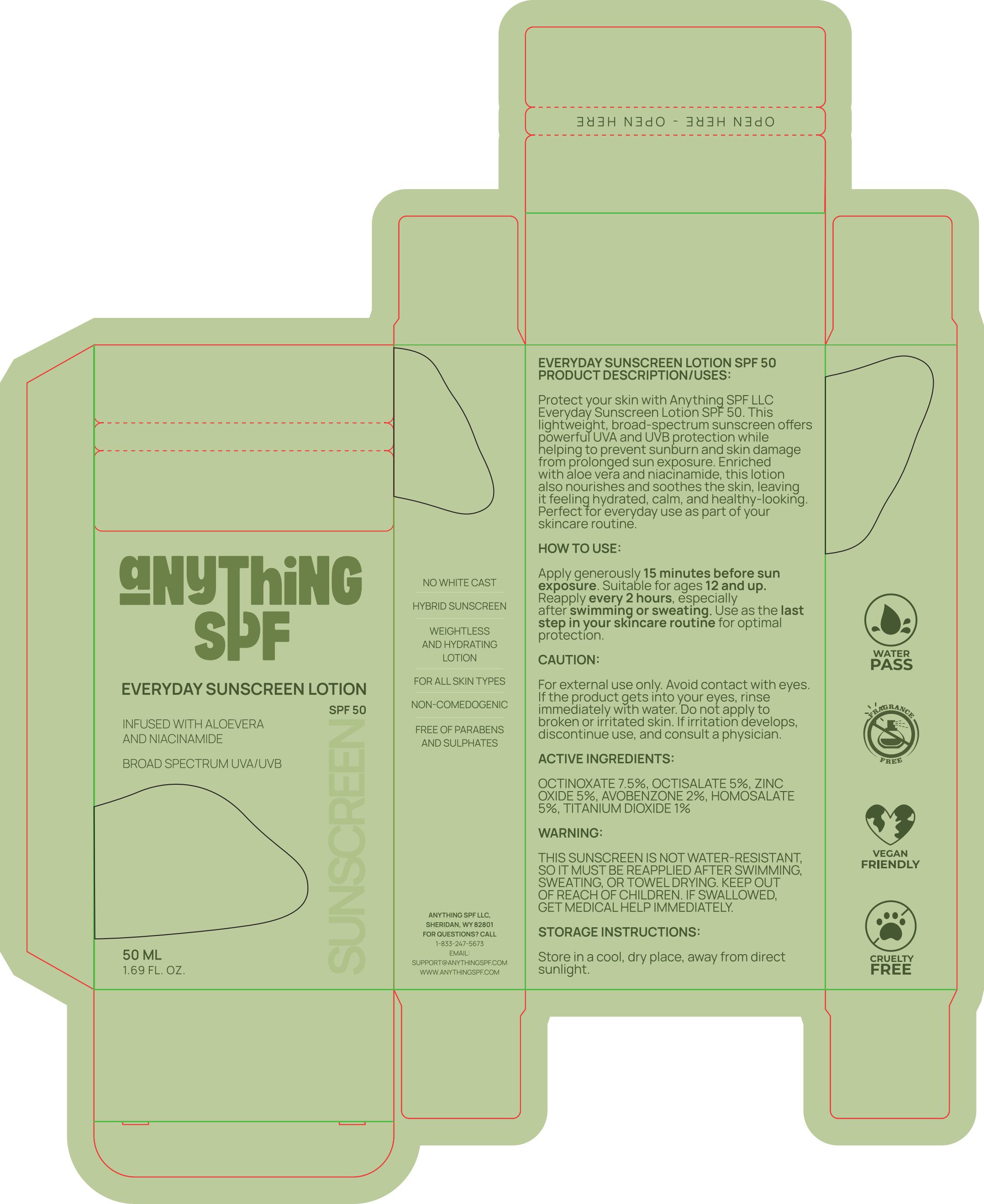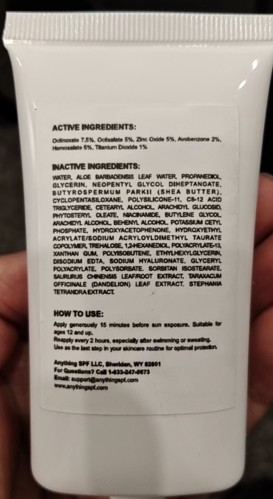 DRUG LABEL: Anything SPF
NDC: 85429-100 | Form: LOTION
Manufacturer: Anything SPF LLC
Category: otc | Type: HUMAN OTC DRUG LABEL
Date: 20250822

ACTIVE INGREDIENTS: OCTINOXATE 7.5 g/100 mL; OCTISALATE 5 g/100 mL; ZINC OXIDE 5 g/100 mL; HOMOSALATE 5 g/100 mL; AVOBENZONE 2 g/100 mL; TITANIUM DIOXIDE 1 g/100 mL
INACTIVE INGREDIENTS: POLYSORBATE 20; POLYACRYLATE-13; SODIUM HYALURONATE; STEPHANIA TETRANDRA ROOT; XANTHAN GUM; HYDROXYETHYL ACRYLATE/SODIUM ACRYLOYLDIMETHYL TAURATE COPOLYMER (100000 MPA.S AT 1.5%); GLYCERYL ACRYLATE/ACRYLIC ACID COPOLYMER (300000 CP AT 2%); CETEARYL ALCOHOL; NIACINAMIDE; WATER; GLYCERIN; BUTYROSPERMUM PARKII (SHEA) BUTTER; ARACHIDYL ALCOHOL; HYDROXYACETOPHENONE; STEARIC ACID; BUTYLENE GLYCOL; PROPANEDIOL; SORBITAN ISOSTEARATE; CYCLOPENTASILOXANE; ARACHIDYL GLUCOSIDE; ETHYLHEXYLGLYCERIN; BEHENYL ALCOHOL; TARAXACUM OFFICINALE LEAF; POTASSIUM CETYL PHOSPHATE; EDETATE DISODIUM; SAURURUS CHINENSIS FLOWER; DIMETHICONE/VINYL DIMETHICONE CROSSPOLYMER (SOFT PARTICLE); TRICAPRIN; NEOPENTYL GLYCOL DIHEPTANOATE; 1,2-HEXANEDIOL; POLYISOBUTYLENE (1300 MW); TREHALOSE; ALOE BARBADENSIS LEAF JUICE

Active Ingredients:

Octinoxate 7.5%, Octisalate 5%, Zinc Oxide 5%, Avobenzone 2%, Homosalate 5%, Titanium Dioxide 1%.

Inactive Ingredients:

WATER, ALOE BARBADENSIS LEAF WATER, PROPANEDIOL, GLYCERIN,
NEOPENTYL GLYCOL DIHEPTANOATE, BUTYROSPERMUM PARKII (SHEA
BUTTER), CYCLOPENTASILOXANE, POLYSILICONE-11, C8-12 ACID TRIGLYCERIDE,
CETEARYL ALCOHOL, ARACHIDYL GLUCOSID, PHYTOSTERYL OLEATE,
NIACINAMIDE, BUTYLENE GLYCOL, ARACHIDYL ALCOHOL, BEHENYL ALCOHOL,
POTASSIUM CETYL PHOSPHATE, HYDROXYACETOPHENONE, HYDROXYETHYL
ACRYLATE/SODIUM ACRYLOYLDIMETHYL TAURATE COPOLYMER, TREHALOSE,
1,2-HEXANEDIOL, POLYACRYLATE-13, XANTHAN GUM, POLYISOBUTENE,
ETHYLHEXYLGLYCERIN, DISODIUM EDTA, SODIUM HYALURONATE, GLYCERYL
POLYACRYLATE, POLYSORBATE, SORBITAN ISOSTEARATE, SAURURUS
CHINENSIS LEAF/ROOT EXTRACT, TARAXACUM OFFICINALE (DANDELION) LEAF
EXTRACT, STEPHANIA TETRANDRA EXTRACT.

How to Use:

- Apply generously 15 minutes before sun exposure
- Suitable for ages 12 and up.
- Reapply every 2 hours especially after swimming or sweating.
- Use as the last step in your skincare routine for optimal protection.

Caution:

For external use only.
Avoid contact with eyes. If the product gets into your eyes, rinse immediately with water.
Do not apply to broken or irritated skin.
If irritation develops, discontinue use, and consult a physician.

Warning:

- This sunscreen is not water-resistant so it must be reapplied after swimming, sweating, or towel drying

Storage Instructions:

Store in a cool, dry place, away from direct sunlight.

Product Description/Usage:

Enriched with aloe vera and niacinamide, this lotion also nourishes and soothes the skin, leaving it feeling hydrated, calm,
and healthy-looking. Perfect for everyday use as part of your skincare routine.

Keep out of reach of children. If swallowed, get medical help immediately.

PURPOSE

Protect your skin with Anything SPF Everyday Sunscreen Lotion SPF 50. This lightweight,
broad-spectrum sunscreen offers powerful UVA and UVB protection while helping to prevent
sunburn and skin damage from prolonged sun exposure.